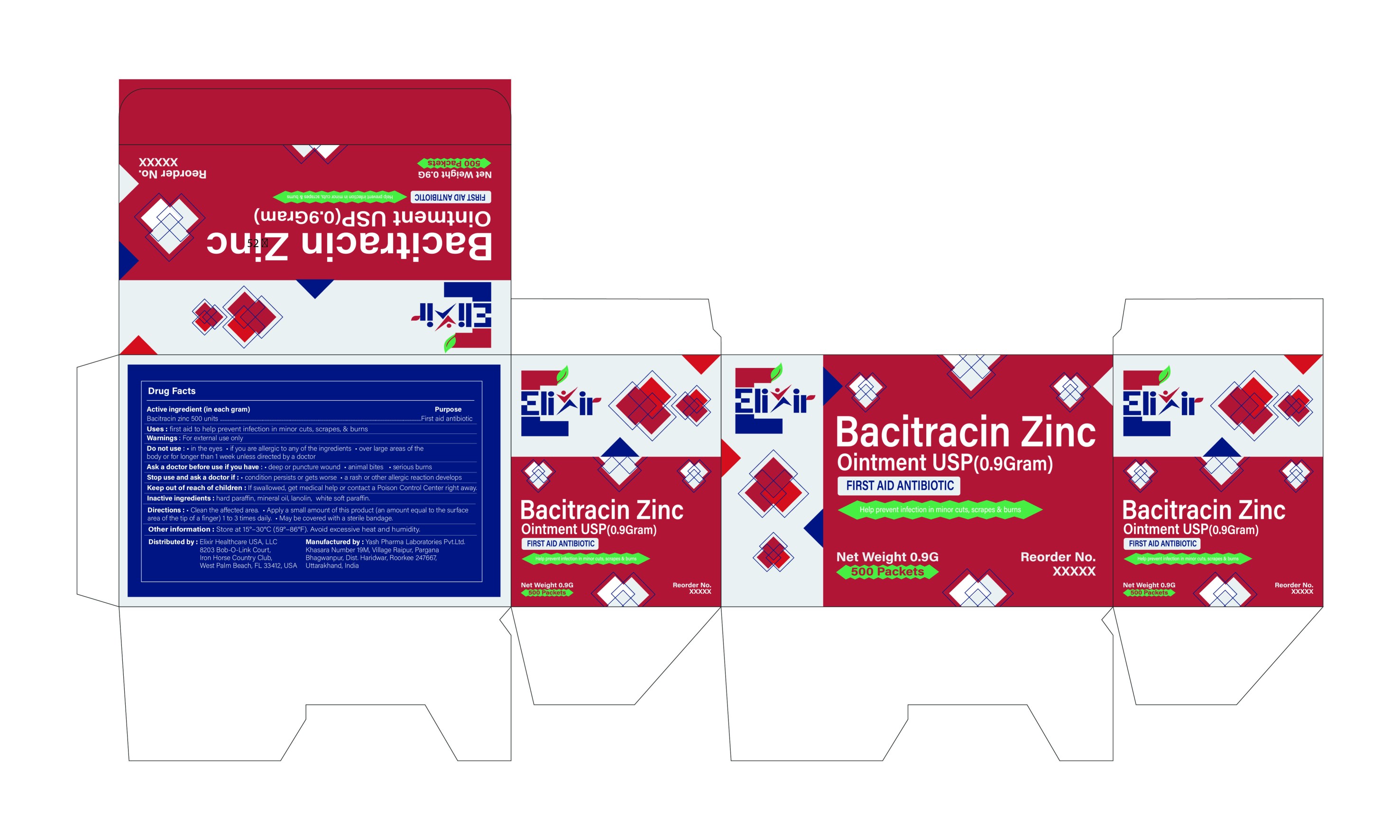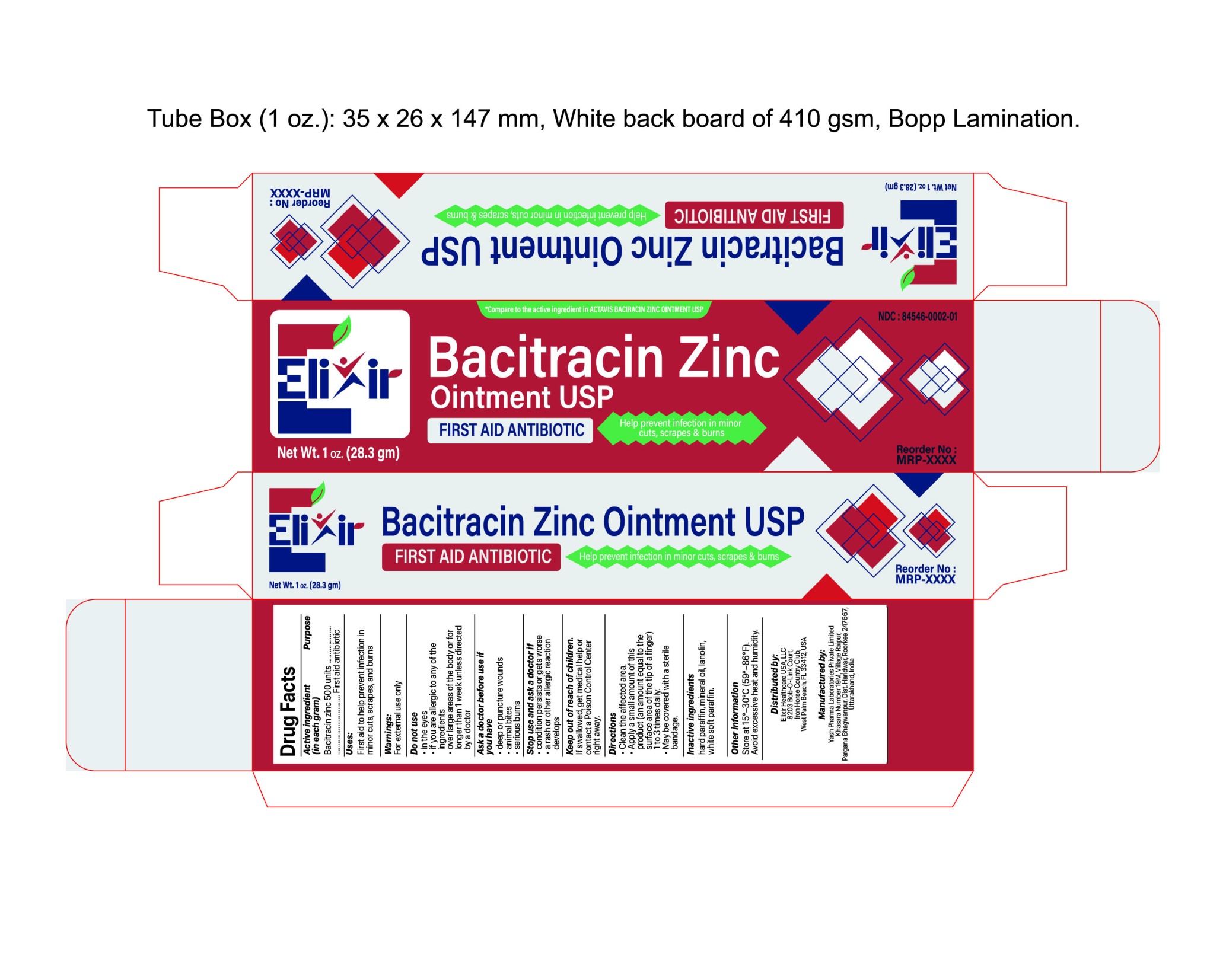 DRUG LABEL: ElixirBaciShield
NDC: 84546-0002 | Form: OINTMENT
Manufacturer: ELIXIR HEALTHCARE USA, LLC.
Category: otc | Type: HUMAN OTC DRUG LABEL
Date: 20251112

ACTIVE INGREDIENTS: BACITRACIN ZINC 500 [USP'U]/1 g
INACTIVE INGREDIENTS: PARAFFIN; MINERAL OIL; WHITE PETROLATUM; LANOLIN

Elixir Bacitracin Zinc Ointment

Active Ingredient (in each gram)

Bacitracin zinc 500 units

Purpose

First Aid Antibiotic

Uses

first aid to help prevent infection in minor cuts, scrapes, and burns

Warnings

For external use only

Do not use

• in the eyes
• if you are allergic to any of the ingredients
• over large areas of the body or for longer than 1 week unless directed by a doctor

Ask a doctor before use in case of

• deep or puncture wounds
• animal bites
• serious burns

Stop use and ask a doctor if

• condition persists or gets worse
• a rash or other allergic reaction develops

Keep out of reach of children

If swallowed, get medical help or contact a Poison Control Center right away.

Directions

• Clean the affected area.
• Apply a small amount of this product (an amount equal to the surface area of the tip of a finger) 1 to 3 times daily.
• May be covered with a sterile bandage.

Inactive ingredients

hard paraffin, mineral oil, lanolin, white soft paraffin.

Other information

Store at 15°–30°C (59°–86°F). Avoid excessive heat and humidity.

PRINCIPAL DISPLAY PANEL

*Compare to the active ingredient in ACTAVIS BACIRACIN ZINC OINTMENT USP

NDC: 84546-0002-01

Bacitracin Zinc Ointment USP

First AID ANTIBIOTIC

Elixir

Net Wt. 1 oz, (28.3 gm)

Help prevent infection in minor cuts, scrapes & burns

Reorder No: MRP-XXXX

PRINCIPAL DISPLAY PANEL

Elixir

Bacitracin Zinc Ointment USP (0.9Gram)

First AID ANTIBIOTIC

Help prevent infection in minor cuts, scrapes & burns

Net Wt. 0.9G, (500 Packets)

Reorder No: MRP-XXXX